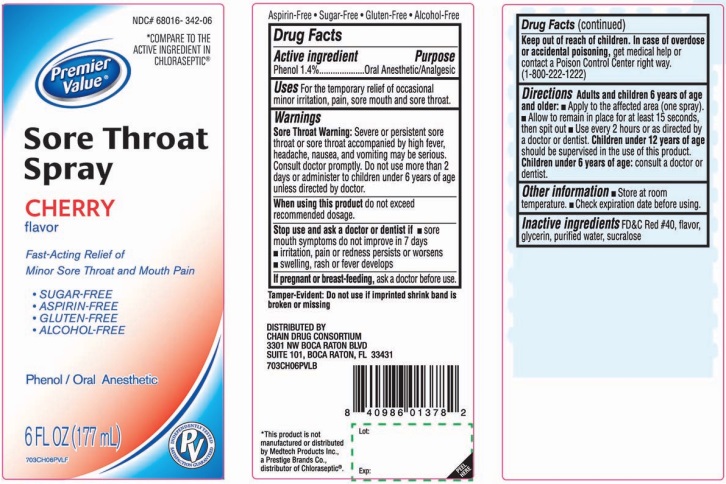 DRUG LABEL: Sore Throat Relief
NDC: 68016-342 | Form: SPRAY
Manufacturer: Chain Drug Consortium
Category: otc | Type: HUMAN OTC DRUG LABEL
Date: 20241028

ACTIVE INGREDIENTS: PHENOL 1.4 g/100 mL
INACTIVE INGREDIENTS: FD&C RED NO. 40; GLYCERIN; WATER; SUCRALOSE

Sore Throat Cherry Flavor Drug Facts

Active ingredient

Phenol 1.4%

Purpose

Oral Anesthetic/Analgesic

Uses

For the temporarily relief of occasional minor irritation, pain, sore mouth, and sore throat.

Warnings

Sore throat warning: Severe or persistent sore throat accompanied by high fever, headache, nausea, and vomiting may be serious. Consult a doctor promptly. Do not use more than 2 days or give to children under 3 years of age.

When using this product,

do not exceed recommended dosage.

Stop use and ask a doctor if

- sore mouth symptoms do not improve in 7 days
- irritation, pain or redness persists or worsens
- swelling, rash or fever develops

If pregnant or breast-feeding,

ask a doctor before use.

Keep out of reach of children.

In case of overdose or accidental poisoning, get medical help or contact a Poison Control Center right away (1-800-222-1222)

Directions

Adults and children 6 years of age and older:

- Apply to the affected area (one spray)
- Allow to remain in place for at least 15 seconds, then spit out
- Use every 2 hours or as directed by a doctor
Children under 12 years of age should be supervised in the use of this product
Children under 6 years of age: consult a doctor or dentist

Other information

- Store at room temperature
- Check expiration date before using

Inactive ingredients

FD&C Red #40, flavor, glycerin, purified water, sucralose

Principal Display Panel

*Compare to the active ingredient in Chloraseptic®*

Sore Throat Relief

Cherry Flavor

Fast acting relief of Minor Sore Throat and Mouth Pain

Phenol/Oral Anesthetic

Sugar-Free

Aspirin-Free

Gluten-Free

Alcohol-Free

6 FL OZ (177 mL)

*This product is not manufactured or distributed by Medtech Products Inc., a Prestige Brands Co., distributor of Chloraseptic®.

Tamper-Evident: Do not use if imprinted shrink band is broken or missing.

DISTRIBUTED BY:

CHAIN DRUG CONSORTIUM LLC.

3301 N.W. BOCA RATON BLVD.

SUITE 101, BOCA RATON FL 33431